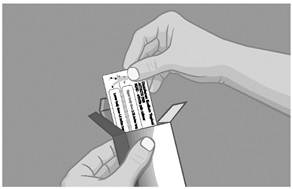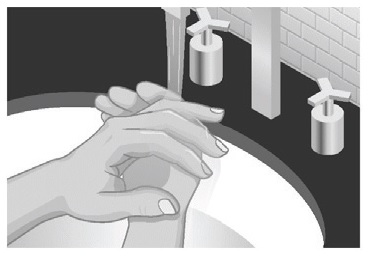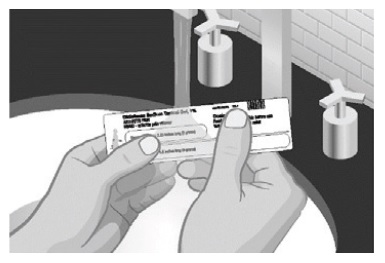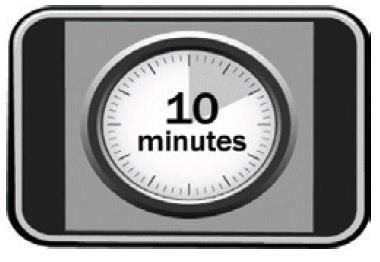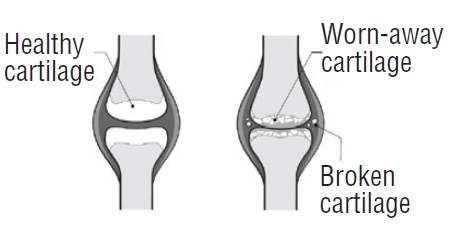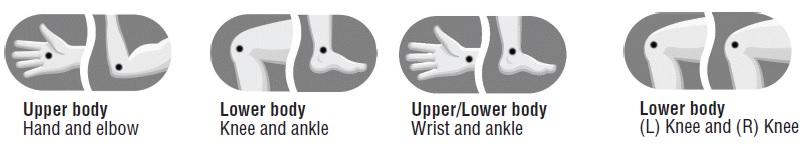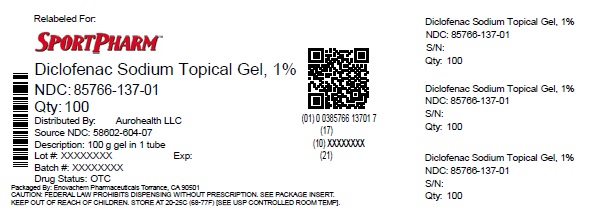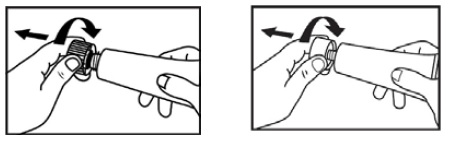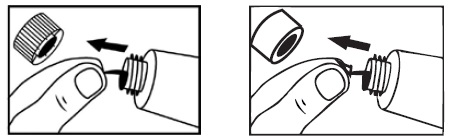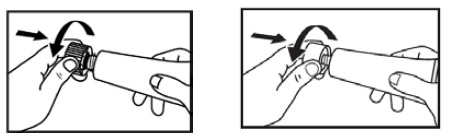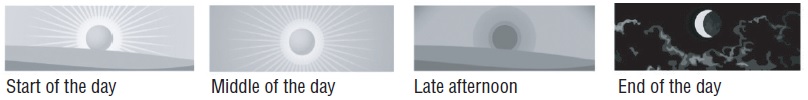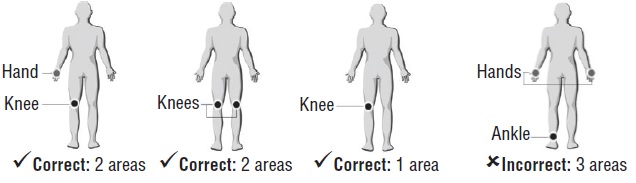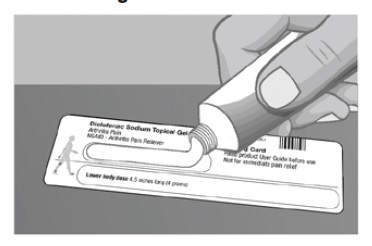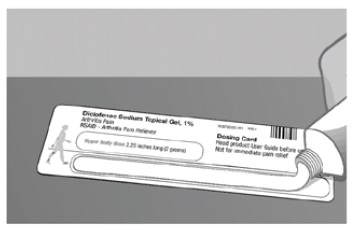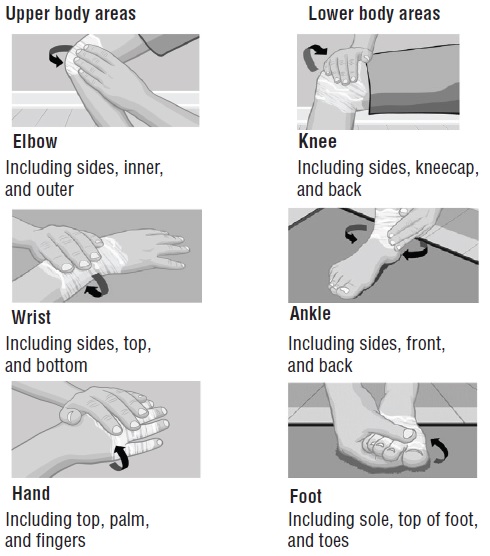 DRUG LABEL: Diclofenac Sodium
NDC: 85766-137 | Form: GEL
Manufacturer: Sportpharm LLC
Category: otc | Type: HUMAN OTC DRUG LABEL
Date: 20260114

ACTIVE INGREDIENTS: DICLOFENAC SODIUM 10 mg/1 g
INACTIVE INGREDIENTS: CARBOMER HOMOPOLYMER TYPE C (ALLYL PENTAERYTHRITOL CROSSLINKED); COCOYL CAPRYLOCAPRATE; ISOPROPYL ALCOHOL; MINERAL OIL; POLYOXYL 20 CETOSTEARYL ETHER; PROPYLENE GLYCOL; WATER; AMMONIA

Drug Facts

Active ingredient
Diclofenac sodium USP (NSAID*) 1% (equivalent to 0.93% diclofenac)
*nonsteroidal anti-inflammatory drug

Purpose

Arthritis pain reliever

Uses

- for the temporary relief of arthritis pain ONLY inthe following areas:
  - hand, wrist, elbow (upper body areas)
  - foot, ankle, knee (lower body areas)
- this product may take up to 7 days to work for arthritis pain; it is not for immediate relief. If no pain relief in 7 days, stop use.

Warnings

For external use only

Allergy alert:Diclofenac may cause a severe allergic reaction, especially in people allergic to aspirin.

Symptoms may include:

- hives
- asthma (wheezing)
- skin reddening
- blisters
- facial swelling
- shock
- rash

If an allergic reaction occurs, stop use and seek medical help right away.
Liver warning: This product contains diclofenac. Liver damage may occur if you apply

- more or for a longer time than directed
- when using other drugs containing diclofenac

Stomach bleeding warning:This product contains an NSAID, which may cause severe stomach bleeding. The chance is small but higher if you

- are age 60 or older
- have had stomach ulcers or bleeding problems
- take a blood thinning (anticoagulant) or steroid drug
- take other drugs containing prescription or nonprescription NSAIDs (aspirin, ibuprofen, naproxen, or others)
- have 3 or more alcoholic drinks every day while using this product
- apply more or for longer than directed

Heart attack and stroke warning:NSAIDs, except aspirin, increase the risk of heart attack, heart failure, and stroke. These can be fatal. The risk is higher if you use more than directed or for longer than directed.

Do not use

- if you have ever had an allergic reaction to any other pain reliever or to a fever reducer
- for strains, sprains, bruises or sports injuries. This product has not been shown to work for these types of injuries.
- right before or after heart surgery
- on more than 2 body areas at the same time
- in the eyes, nose or mouth

Ask a doctor before use if

- you have problems or serious side effects from taking pain relievers or fever reducers
- stomach bleeding warning applies to you
- you have a history of stomach problems, such as heartburn
- you have high blood pressure, heart disease, liver cirrhosis, kidney disease, asthma, or had a stroke
- you are taking a diuretic
- you are under age 18 years. It is not known if this drug works or is safe in children under age 18 years.

Ask a doctor or pharmacist before use if you are

- under a doctor’s care for any serious condition
- taking any other drug

When using this product

- avoid contact with eyes, nose, or mouth
- if eye contact occurs, rinse thoroughly with water

Stop use and ask a doctor if

- pain gets worse or lasts more than 21 days
- redness or swelling is present in the painful area
- fever occurs
- skin irritation occurs
- any new symptoms appear. These could be signs of a serious condition.
- you experience any of the following signs of stomach bleeding:
  - feel faint
  - have bloody or black stools
  - vomit blood
  - have stomach pain that does not get better
- you have symptoms of heart problems or stroke:
  - chest pain
  - trouble breathing
  - leg swelling
  - weakness in one part or side of body
  - slurred speech

If pregnant or breast-feeding,

ask a health professional before use. It is especially important not to use diclofenac at 20 weeks or later in pregnancy unless definitely directed to do so by a doctor because it may cause problems in the unborn child or complications during delivery.

Keep out of reach of children.

If swallowed, get medical help or contact a Poison Control Center right away.

Directions

Use up to 21 days unless directed by your doctor

Not for strains, sprains, bruises or sports injuries. This product has not been shown to work for these types of injuries.

Daily | Per Dose
For your arthritis pain:; - Use 4 times per day every day - Do not use on more than 2 body areas at the same time | Use ENCLOSED DOSING CARD to measure a dose; - For each upper body area (hand, wrist, or elbow) - Squeeze out 2.25 inches (2 grams) - For each lower body area (foot, ankle or knee) - Squeeze out 4.5 inches (4 grams)

Read the enclosed User Guidefor complete instructions:

- use only as directed
- do not use more than directed or for longer than directed
- apply only to clean, dry skin that does not have any cuts, open wounds, infections or rashes
- do not apply in same area as any other product
- do not apply with external heat such as heating pad
- do not apply a bandage over the treated area
- store ENCLOSED DOSING CARD with your diclofenac sodium topical gel arthritis pain. The dosing card is re-usable.

Other information

- store at 20° to 25°C (68° to 77°F). Keep from freezing.
- read all product information before using. Keep the dosing card, this carton and accompanying User Guide for important information.

Inactive ingredients

carbomer homopolymer Type C, cocoyl caprylocaprate, fragrance, isopropyl alcohol, mineral oil, polyoxyl 20 cetostearyl ether, propylene glycol, purified water, strong ammonia solution

Questions or comments?call 1-855-274-4122

Distributed by:
AUROHEALTH LLC
279 Princeton-Hightstown Road
East Windsor, NJ 08520
Made in India
Code: TS/DRUGS/58039/2020

DICLOFENAC SODIUM TOPICAL GEL, 1% Arthritis Pain
NSAID – Arthritis Pain Reliever User Guide
How to use diclofenac sodium topical gel arthritis pain, with answers to frequently asked questions
Quick Start
How to get started right away with diclofenac sodium topical gel arthritis pain
Understanding Diclofenac Sodium Topical Gel Arthritis Pain
Diclofenac sodium topical gel arthritis pain (diclofenac sodium topical gel, 1% (NSAID)- arthritis pain reliever) is an arthritis pain relief medication that you apply to your skin. It is intended to be used 4 times a day every day for up to 21 days.
Before You Use Diclofenac Sodium Topical Gel Arthritis Pain
Read the Drug Facts Label, which appears on the carton.
Remove the dosing card from the inside of the carton. You should always use the dosing card to measure out the correct dose of diclofenac sodium topical gel arthritis pain.
The first time you use a tube of diclofenac sodium topical gel arthritis pain:
You will have either one of the caps shown below.
1. Take the cap off the tube.

2. Lift tab and pull to remove foil seal prior to use. Do not open the safety seal with the scissors or other sharp objects.

3. After use, put the cap back on the end of the tube.

Using Diclofenac Sodium Topical Gel Arthritis Pain
How often to use diclofenac sodium topical gel arthritis pain
Use 4 times a day for best results.
For example:
Where to apply diclofenac sodium topical gel arthritis pain
Diclofenac sodium topical gel arthritis pain can be used on up to 2 body areas from the following list: a hand, a wrist, an elbow, a foot, an ankle, a knee. Do not use on more than 2 body areas at once.
Some examples include:
Measuring the correct amount using the dosing card
For each upper body area(a hand, a wrist, or an elbow):
Squeeze gel from the tube equal to the length shown on the upper body section of the dosing card (2.25 inches).
For each lower body area(a foot, an ankle, or a knee):
Squeeze gel from the tube equal to the length shown on the lower body section of the dosing card (4.5 inches).
Lost Your Dosing Card? Don’t worry! Call 1-855-274-4122 to get a free replacement.
Applying Diclofenac Sodium Topical Gel Arthritis Pain
Gently rub diclofenac sodium topical gel arthritis pain into the skin using your hand. Apply 4 times a day for best results. Do not use on more than 2 body areas at once.
Apply only to clean, dry skin that doesn’t have any cuts, open wounds, infections or rashes. Do not apply in the same area as any other medicines or products that are applied to the skin.
After You Use Diclofenac Sodium Topical Gel Arthritis Pain
Wash your hands after applying diclofenac sodium topical gel arthritis pain.
If the treated area is the hands wait up to 1 hour to wash the hands.
Wash the dosing card with water. Store dosing card with your diclofenac sodium topical gel arthritis pain and keep out of reach of children.
Wait ten minutesbefore covering the treated areas with clothes or gloves.
Avoid:

- showering or bathing for at least 1 hour after use
- exposing the treated area to sunlight or artificial light (such as in tanning booths)
- use in same area as other products applied to the skin
- applying a bandage over the treated area
- eye, nose, or mouth contact. If eye contact occurs, rinse thoroughly with water.

Facts you need to know
Important information about diclofenac sodium topical gel arthritis pain
Do not use diclofenac sodium topical gel arthritis pain...

- if you have ever had an allergic reaction to any other pain reliever or to a fever reducer
- for strains, sprains, bruises or sports injuries. This product has not been shown to work for these types of injuries.
- right before or after heart surgery
- on more than 2 body areas at the same time
- in the eyes, nose or mouth

Ask a doctor before use if...

- you have problems or serious side effects from taking pain relievers or fever reducers
- stomach bleeding warning applies to you
- you have a history of stomach problems such as heartburn
- you have high blood pressure, heart disease, liver cirrhosis, kidney disease, asthma, or had a stroke
- you are taking a diuretic
- you are under age 18 years. It is not known if this drug works or is safe in children under age 18 years.

Ask a doctor or pharmacist before use if...

- you are under a doctor’s care for any serious condition
- you are taking any other drug
- you are pregnant or breast-feeding

It is especially important not to use diclofenac at 20 weeks or later in pregnancy unless definitely directed to do so by a doctor because it may cause problems in the unborn child or complications during delivery.
Warnings to consider before use…
Allergy alertDiclofenac may cause a severe allergic reaction, especially in people allergic to aspirin. Symptoms may include:

- hives
- asthma (wheezing)
- skin reddening
- rash
- blisters
- facial swelling
- shock

If an allergic reaction occurs, stop use and seek medical help right away.
Liver warning
This product contains diclofenac. Liver damage may occur if you apply

- more or for a longer time than directed
- when using other drugs containing diclofenac

Stomach bleeding warningThis product contains an NSAID, which may cause stomach bleeding. The chance is small but higher if you

- are age 60 or older
- have had stomach ulcers or bleeding problems
- take a blood thinning (anticoagulant) or steroid drug
- take other drugs containing prescription or nonprescription NSAIDs (aspirin, ibuprofen, naproxen, or others)
- have 3 or more alcoholic drinks every day while using this product
- apply more or for longer than directed

Heart attack and stroke warningNSAIDs, except aspirin, increase the risk of heart attack, heart failure, and stroke. This can be fatal. The risk is higher if you use more than directed or for longer than directed.
Follow these important guidelines when usingdiclofenac sodium topical gel arthritis pain...

- use only as directed
- apply only to clean, dry skin that does not have any cuts, open wounds, infections or rashes
- do not apply in same area as any other product used on the skin
- do not apply with external heat such as heating pad
- do not apply a bandage over the treated area
- do not get gel in eyes, nose or mouth
- store ENCLOSED DOSING CARD with your diclofenac sodium topical gel arthritis pain. The dosing card is re-usable.

Keep out of reach of children.
If swallowed, get medical help or contact a Poison Control Center right away.
Stop using diclofenac sodium topical gel arthritis pain and ask a doctor if...

- pain gets worse or lasts more than 21 days
- redness or swelling is present in the painful area
- fever occurs
- skin irritation occurs
- any new symptoms appear. These could be signs of a serious condition.
- you experience any of the following signs of stomach bleeding:
  - feel faint
  - have bloody or black stools
  - vomit blood
  - have stomach pain that does not get better
- you have symptoms of heart problems or stroke:
  - chest pain
  - trouble breathing
  - leg swelling
  - weakness in one part or side of body
  - slurred speech

Questions and Answers
Answers to questions you may ask about diclofenac sodium topical gel arthritis pain
Can I use diclofenac sodium topical gel arthritis pain for the immediate relief of pain like that associated with sprains, strains, bruises or sports injuries? No.Do not use for strains, sprains, bruises, or sports injuries. This product has not been shown to work for these types of injuries. It’s intended only for the temporary relief of arthritis pain.
How quickly will diclofenac sodium topical gel arthritis pain work for arthritis pain? Diclofenac sodium topical gel arthritis pain may take up to 7 days to work for your arthritis pain; it is not for immediate relief. With 4 times-a-day use, you may start to feel relief within a few days. You should feel significant pain relief within 7 days of continuous use. If no pain relief in 7 days, stop use.
What is diclofenac sodium topical gel arthritis pain used for? Diclofenac sodium topical gel arthritis pain can be used for the temporary relief of arthritis pain in the hands, wrists, elbows, feet, ankles, and knees. Osteoarthritis (OA) is the most common form of arthritis. It mainly affects a type of tissue called cartilage, which cushions the joints and prevents the bones from rubbing against each other.
With OA, cartilage begins to break down and wear away, resulting in joint pain and stiffness. OA occurs more frequently as you get older. Pain develops slowly and can gradually worsen over time.
How does diclofenac sodium topical gel arthritis pain work? Diclofenac sodium, the medicine in diclofenac sodium topical gel arthritis pain, is a nonsteroidal anti-inflammatory drug (NSAID). NSAIDs are used to treat pain from medical conditions such as arthritis. Diclofenac sodium topical gel arthritis pain works similarly to oral NSAIDs like ibuprofen or naproxen by temporarily blocking the production of pain signaling chemicals called prostaglandins. However, when taking a pill, the medication is distributed to the site of pain through the bloodstream. Compared to oral diclofenac, only 6% of the medicine in diclofenac sodium topical gel arthritis pain is absorbed in the bloodstream. It works by penetrating through your skin at the application site to deliver arthritis pain relief.
How does over-the-counter diclofenac sodium topical gel arthritis pain differ from prescription diclofenac sodium topical gel? Over-the-counter diclofenac sodium topical gel arthritis pain is the same strength and formula as original full prescription strength diclofenac sodium topical gel but is available without a prescription.
Apply diclofenac sodium topical gel arthritis pain 4 times a day to ensure you get the full effect of the medicine.
Can I apply diclofenac sodium topical gel arthritis pain to upper and lower body areas at the same time? Yes.You can use diclofenac sodium topical gel arthritis pain on up to 2 body areas at the same time. The areas can include the foot, ankle, knee, hand, wrist, and elbow.
Some correct examples include:
Do not use diclofenac sodium topical gel arthritis pain on more than 2 body areas at once.
Can I apply diclofenac sodium topical gel arthritis pain without measuring it out on the dosing card first? No.Use the dosing card to make sure you are getting the correct amount of medicine.
Can I use diclofenac sodium topical gel arthritis pain on my spine, hips, or shoulders? No.The use of diclofenac sodium topical gel arthritis pain on the spine, hips, and shoulders has not been studied.
Can I take any other pain medications with diclofenac sodium topical gel arthritis pain? Ask your doctor or pharmacist before using diclofenac sodium topical gel arthritis pain if you are taking any other pain reliever or are planning on taking any other pain reliever, especially prescription or nonprescription NSAIDs (aspirin, ibuprofen, naproxen, or others).
Can I take any other pain medications during the first 7 days I use diclofenac sodium topical gel arthritis pain? Taking other pain medications is generally not recommended. Speak with your doctor or pharmacist before taking other pain medications when using diclofenac sodium topical gel arthritis pain.
How long can I use diclofenac sodium topical gel arthritis pain? Use diclofenac sodium topical gel arthritis pain 4 times a day every day for up to 21 days for treatment of arthritis pain or as directed by your doctor.
Diclofenac sodium topical gel arthritis pain should be part of an overall program for managing your arthritis pain. The program should also include activities such as appropriate movement or exercise, specific lifestyle changes, and weight maintenance. Regular visits and discussions with your doctor can help incorporate diclofenac sodium topical gel arthritis pain into a complete program to help manage your arthritis pain.
What do I do if I get diclofenac sodium topical gel arthritis pain in my eyes? If eye contact occurs, rinse thoroughly with water and consult a doctor if irritation lasts more than an hour.
How do I clean the dosing card? Wash the dosing card with water, and store dosing card and tube out of reach of children.
What if I miss a dose of diclofenac sodium topical gel arthritis pain? If you forget to apply diclofenac sodium topical gel arthritis pain, don’t double your dose. Just apply the next dose as scheduled.
How should I store diclofenac sodium topical gel arthritis pain?

- Store at 20° to 25°C (68° to 77°F).
- Do not freeze diclofenac sodium topical gel arthritis pain.
- Store the dosing card with your diclofenac sodium topical gel arthritis pain.
- Keep out of reach of children.

Helpful Tip: If you forget to apply diclofenac sodium topical gel arthritis pain, don't double your dose. Just apply the next dose as scheduled.
Additional Questions?
Call 1-855-274-4122
Distributed by:

Sportpharm

2237 N Commerce Parkway,

STE 1, Weston, Florida-33326

Relabeled by:

Enovachem PHARMACEUTICALS

Torrance, CA 90501

PACKAGE LABEL-PRINCIPAL DISPLAY PANEL - 1% w/w tube Label (100 g Tube)

ORIGINAL PRESCRIPTION STRENGTH
Diclofenac Sodium ††Compare to Voltaren® Arthritis Pain
Topical Gel, 1% Active Ingredient
Arthritis Pain
NSAID - Arthritis Pain Reliever FOR EXTERNAL USE ONLY
Anti-Inflammatory Net Wt. 3.53 oz (100 g)